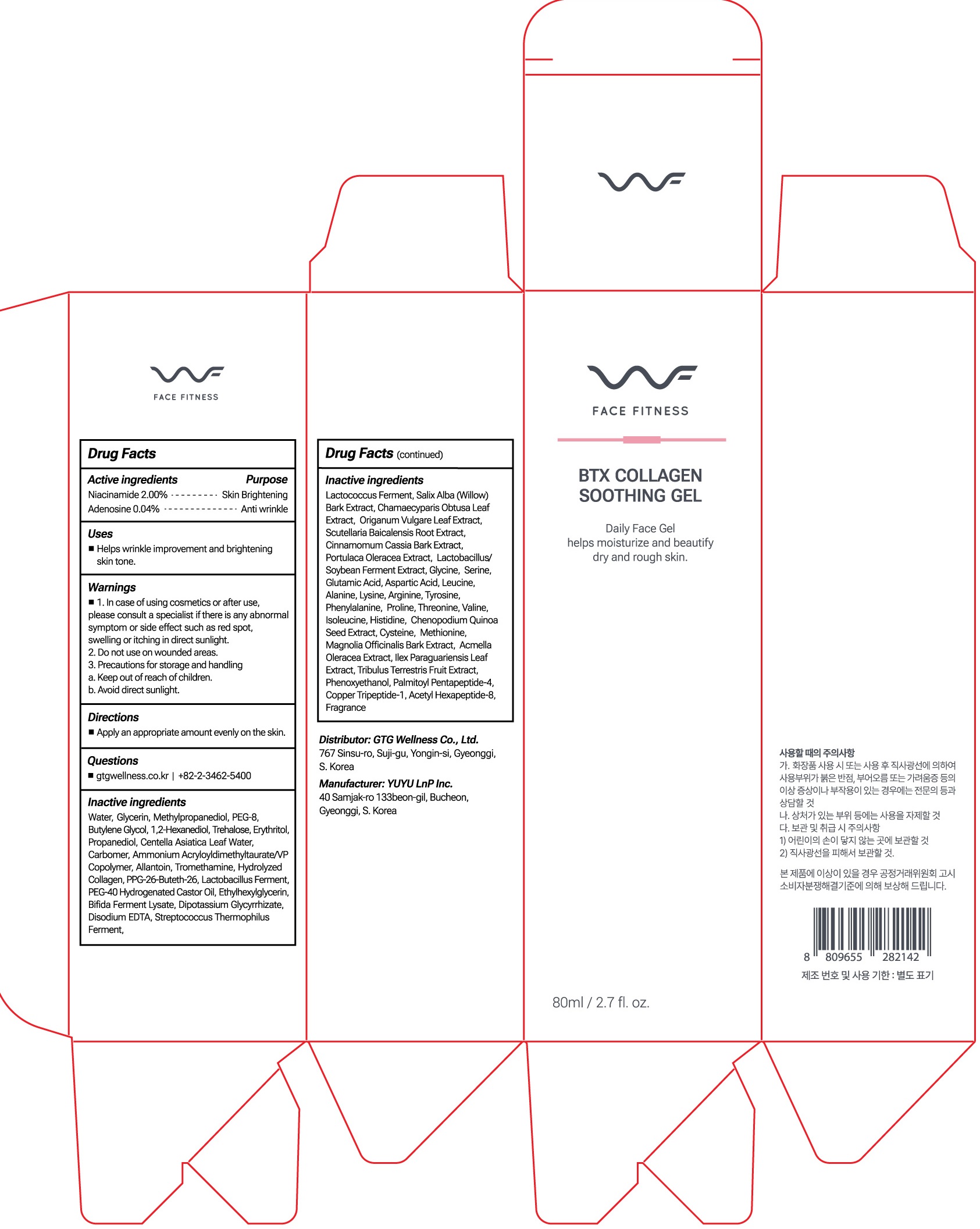 DRUG LABEL: WF FACE FITNESS BTX COLLAGEN SOOTHING
NDC: 71080-0032 | Form: GEL
Manufacturer: GTG WELLNESS CO., LTD.
Category: otc | Type: HUMAN OTC DRUG LABEL
Date: 20230630

ACTIVE INGREDIENTS: Niacinamide 2.00 g/100 mL; Adenosine 0.04 g/100 mL
INACTIVE INGREDIENTS: Water; Glycerin; Methylpropanediol; Butylene Glycol

ACTIVE INGREDIENT

Niacinamide 2.00%
Adenosine 0.04%

INACTIVE INGREDIENTS

Water, Glycerin, Methylpropanediol, PEG-8, Butylene Glycol, 1,2-Hexanediol, Trehalose, Erythritol, Propanediol, Centella Asiatica Leaf Water, Carbomer, Ammonium Acryloyldimethyltaurate/VP Copolymer, Allantoin, Tromethamine, Hydrolyzed Collagen, PPG-26-Buteth-26, Lactobacillus Ferment, PEG-40 Hydrogenated Castor Oil, Ethylhexylglycerin, Bifida Ferment Lysate, Dipotassium Glycyrrhizate, Disodium EDTA, Streptococcus Thermophilus Ferment, Lactococcus Ferment, Salix Alba (Willow) Bark Extract, Chamaecyparis Obtusa Leaf Extract, Origanum Vulgare Leaf Extract, Scutellaria Baicalensis Root Extract, Cinnamomum Cassia Bark Extract, Portulaca Oleracea Extract, Lactobacillus/Soybean Ferment Extract, Glycine, Serine, Glutamic Acid, Aspartic Acid, Leucine, Alanine, Lysine, Arginine, Tyrosine, Phenylalanine, Proline, Threonine, Valine, Isoleucine, Histidine, Chenopodium Quinoa Seed Extract, Cysteine, Methionine, Magnolia Officinalis Bark Extract, Acmella Oleracea Extract, Ilex Paraguariensis Leaf Extract, Tribulus Terrestris Fruit Extract, Phenoxyethanol, Palmitoyl Pentapeptide-4, Copper Tripeptide-1, Acetyl Hexapeptide-8, Fragrance

PURPOSE

Skin Brightening
Anti wrinkle

WARNINGS

1. In case of using cosmetics or after use, please consult a specialist if there is any abnormal symptom or side effect such as red spot, swelling or itching in direct sunlight. 2. Do not use on wounded areas.
3. Precautions for storage and handling a. Keep out of reach of children. b. Avoid direct sunlight.

KEEP OUT OF REACH OF CHILDREN

Uses

■ Helps wrinkle improvement and brightening skin tone.

Directions

■ Apply an appropriate amount evenly on the skin.

Questions

■ gtgwellness.co.kr | +82-2-3462-5400